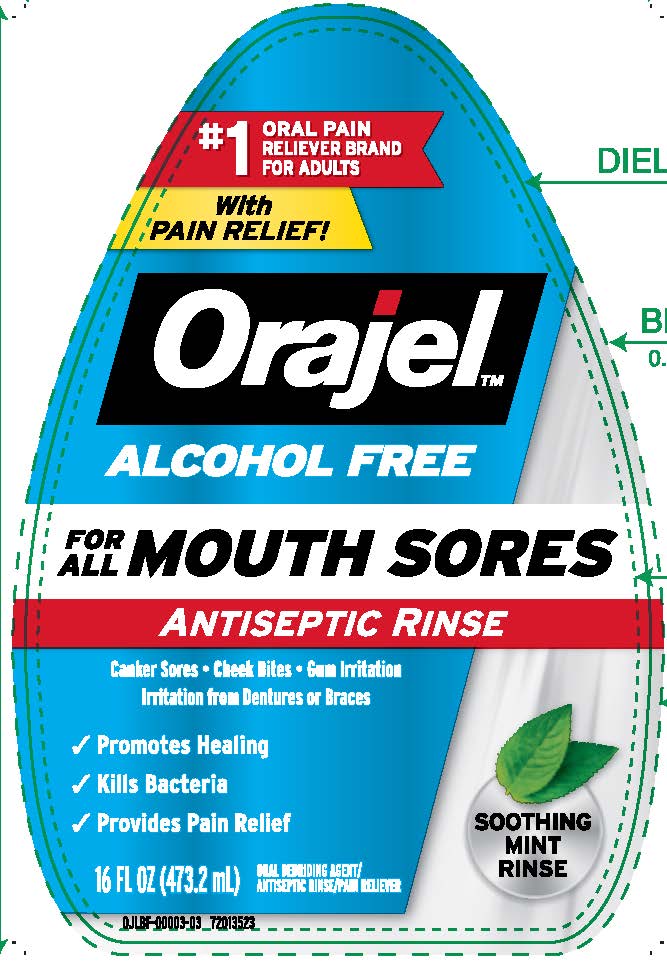 DRUG LABEL: Orajel Antiseptic Alcohol-Free Mouth Sore Rinse
NDC: 10237-784 | Form: LIQUID
Manufacturer: Church & Dwight Co., Inc.
Category: otc | Type: HUMAN OTC DRUG LABEL
Date: 20241127

ACTIVE INGREDIENTS: MENTHOL, UNSPECIFIED FORM 1 mg/1 mL; HYDROGEN PEROXIDE 15 mg/1 mL
INACTIVE INGREDIENTS: SORBITOL; WATER; SACCHARIN SODIUM; EDETATE DISODIUM; PROPYLENE GLYCOL; FD&C BLUE NO. 1; METHYL SALICYLATE; PHOSPHORIC ACID; POLOXAMER 338; POLYSORBATE 20

Orajel Antiseptic Alcohol-Free Mouth Sore Rinse

Active ingredients

Hydrogen peroxide 1.5%

Menthol 0.1%

Purpose

Oral debriding agent/Oral antiseptic, Oral pain reliever

Uses

- first aid to help reduce bacteria in minor oral wounds
- for temporary pain relief and
- use in cleansing minor wounds or minor gum inflammation resulting from:
  - minor dental procedures
  - orthodontic appliances
  - dentures
  - accidental injury
  - canker sores
  - other irritations of the mouth and gums

Aids in the removal of:

- phlegm
- mucus
- other secretions associated with occasional sore mouth

Warnings

Do not usethis product for more than 7 days unless directed by a dentist or healthcare provider

When using this product

- do not swallow
- do not exceed recommended dosage

Stop Use

Stop Use and see your physician promptly if

- swelling, rash or fever develops
- irritations, pain or redness persists or worsens
- sore mouth symptoms do not improve in 7 days

Keep out of reach of children

If more than used for rinsing is accidentally swallowed, get medical help or contact a poison Control Center right away

Directions

Adults and children 2 years of age and older

- Swish one-half capful (2 tesapoons=10mL) around the mouth over the affected area for at least 1 minute and then spit out. Use up to 4 times daily after meals and at bedtime or as directed by a dentist or healthcare provider

Children under 12 years of age

- Should be supervised in the use of this product

Children under 2 years of age

- Consult a dentist or healthcare provider

Other information

- cap tightly
- keep away from heat or direct sunlight
- do not use if safety seal is broken or missing

Inactive ingredients

blue 1, disodium EDTA, methyl salicylate, phosphoric acid, poloxamer 338, polysorbate 20, propylene glycol, sodium saccharin, sorbitol, water

Questions or comments call us at 1–800–952–5080 M–F 9am–5pm ET or visit our website at www.orajel.com

Principal Display Panel

#1 ORAL PAIN RELIEVER BRAND FOR ADULTS

With PAIN RELIEF!

Orajel

ALCOHOL FREE

FOR ALL MOUTH SORES

ANTISEPTIC RINSE

Canker Sores Cheek Bites Gum Irritation Irritation from Dentures or Braces

Promotes Healing

Kills Bacteria

Provides Pain Relief

SOOTHING MINT RINSE

16 FL OZ (473.2 mL)

ORAL DEBRIDING AGENT/ANTISEPTIC RINSE/PAIN RELIEVER